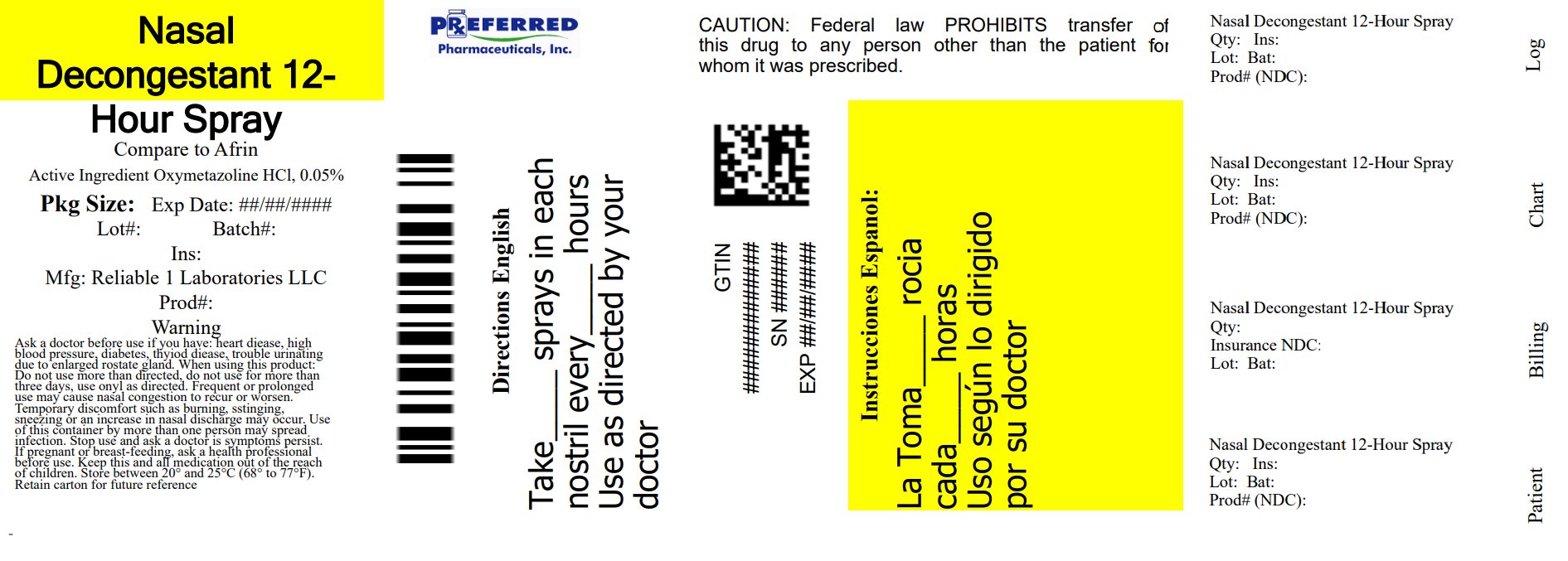 DRUG LABEL: Oxymethazoline HCL
NDC: 68788-7516 | Form: SPRAY
Manufacturer: Preferred Pharmaceuticals Inc.
Category: otc | Type: HUMAN OTC DRUG LABEL
Date: 20250818

ACTIVE INGREDIENTS: OXYMETAZOLINE HYDROCHLORIDE 0.05 mg/1 1
INACTIVE INGREDIENTS: SODIUM PHOSPHATE, MONOBASIC, ANHYDROUS; EDETATE SODIUM; PROPYLENE GLYCOL; BENZALKONIUM CHLORIDE; SODIUM PHOSPHATE, DIBASIC, ANHYDROUS; POLYETHYLENE GLYCOL, UNSPECIFIED; WATER; POVIDONE, UNSPECIFIED

12 Hour Decongestant Nasal Spray

Active ingredient

Oxymetazoline HCL 0.05%

Purpose

Nasal decongestant

Uses

temporarily relieves nasal congestion due to:

- common cold

- hay fever

- upper respiratory allergies

temporarily relieves sinus congestion and pressure

shrinks swollen nasal membranes

Ask a doctor before use if you have

heart disease

high blood pressure

thyroid disease

diabetes

trouble urinating due to an enlarged prostate gland

Stop use and ask a doctor if symptoms presist

PREGNANCY OR BREAST FEEDING

If pregnant or breast-feeding, ask a health professional before use.

Keep out of reach of children. If swallowed, get medical help or contact a Poison Control Center right away.

Directions

adults and children 6 to under 12 years of age (with adult supervision): 2 or 3 sprays in each nostril. Not more often than every 10-12 hours. Do not exceed 2 doeses in 24 hours.

children under 6 years of age: ask a doctor.

Instructions for use: Shake well before use. to open, rotate cap to align the marks. Squeeze cap on toh sides in a counter-clockwise turn and pull to remove. To spray, hold bottles with thumb at base and nozzle between first and second fingers. Without tilting the head, insert nozzle into nostril. Fully depress rim with a firm even stroke and sniff deeply. Wipe nozzle clean after use and snap cap back onto bottle.

Other information

store between 20º to 25º C (68º to 77º F)

retain carton for future referance on full labeling

Inactive ingredients

benzalkoium cjloride, dibasic sodium phosphate, edetate disodium dihydrate, monobasic sodium phosphate, polyethylene glycol, propylene glycol, povidone, purified water

Questions or comments?

call 516-341-0666, 8:30 am - 4:30 pm ET, Monday - Friday

Warnings

Ask a doctor before use if you have

heart disease

high blood pressure

thyroid disease

diabetes

trouble urinating due to an enlarged prostate gland

When using this prduct

do not use more than directed

do not use more than 3 days. Use only as directed. Frequent or prolonged use may cause nasal congestion to recur or worsen.

temporary discomfort such as burning, stinging, sneexing, or an increased nasal discharge may occur

use of this container by more than one person may spread infection

PACKAGE LABEL

NDC 68788-7516-3

Reliabel-1 Laboratories

12 Hour Decongestant Nasal Spray

Oxymetazoline HCL

Pump Mist Anti-Drip

Rapid & Powerful

Congestion Relief

12 Hour Relief

1 FL OZ (30 mL)

Relabeled By: Preferred Pharmaceuticals Inc.